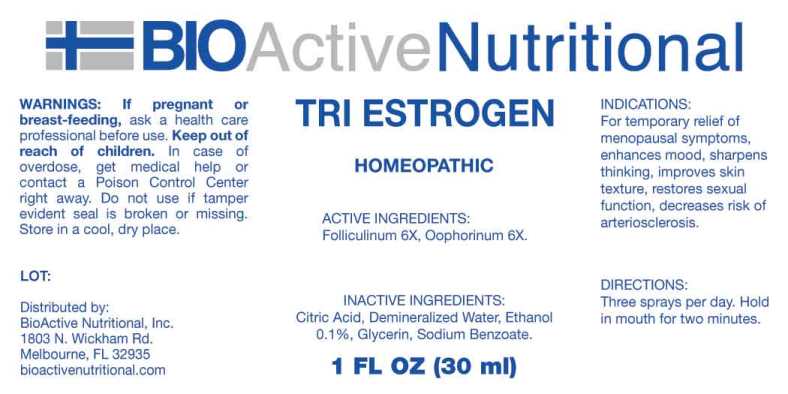 DRUG LABEL: Tri Estrogen
NDC: 43857-0036 | Form: SPRAY
Manufacturer: BioActive Nutritional
Category: homeopathic | Type: HUMAN OTC DRUG LABEL
Date: 20240912

ACTIVE INGREDIENTS: ESTRONE 6 [hp_X]/1 mL; SUS SCROFA OVARY 6 [hp_X]/1 mL
INACTIVE INGREDIENTS: CITRIC ACID MONOHYDRATE; GLYCERIN; SODIUM BENZOATE; WATER; ALCOHOL

DRUG FACTS:

ACTIVE INGREDIENTS:

Folliculinum 6X, Oophorinum 6X.

INDICATIONS:

For temporary relief of menopausal symptoms, enhances mood, sharpens thinking, improves skin texture, restores sexual function, decreases risk of arteriosclerosis.

WARNINGS:

If pregnant or breast-feeding, ask a health care professional before use.

Keep out of reach of children. In case of overdose, get medical help or contact a Poison Control Center right away.

Do not use if tamper evident seal is broken or missing.

Store in a cool, dry place.

KEEP OUT OF REACH OF CHILDREN:

In case of overdose, get medical help or contact a Poison Control Center right away.

DIRECTIONS:

Three sprays per day. Hold in mouth for two minutes.

INDICATIONS:

For temporary relief of menopausal symptoms, enhances mood, sharpens thinking, improves skin texture, restores sexual function, decreases risk of arteriosclerosis.

INACTIVE INGREDIENTS:

Citric Acid, Demineralized Water, Ethanol 0.1%, Glycerin, Sodium Benzoate.

QUESTIONS

Distributed by:
BioActive Nutritional, Inc.
1803 N. Wickham Rd.
Melbourne, FL 32935
bioactivenutritional.com

PACKAGE LABEL DISPLAY:

BIOActive Nutritional

TRI ESTROGEN

HOMEOPATHIC

1 FL OZ (30 ml)